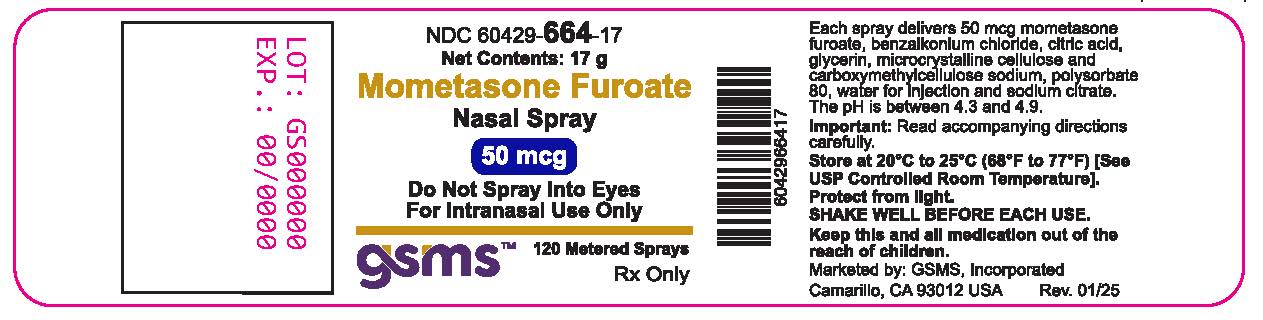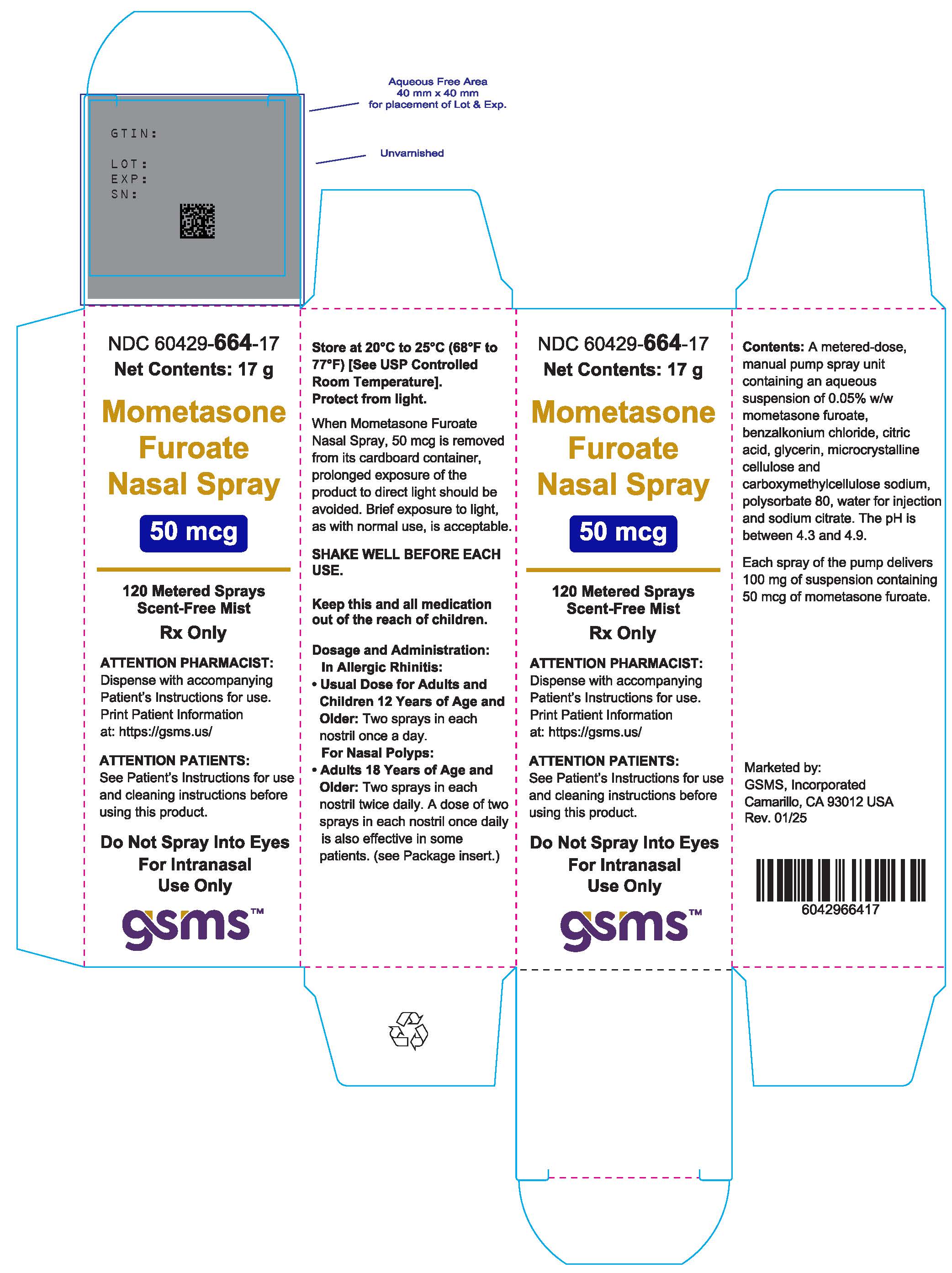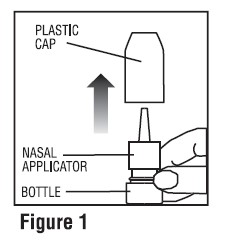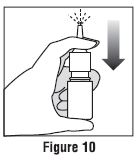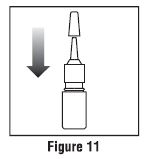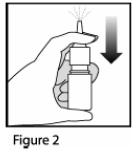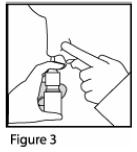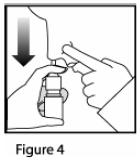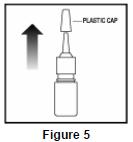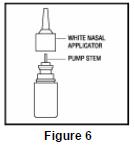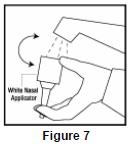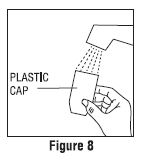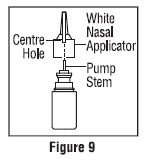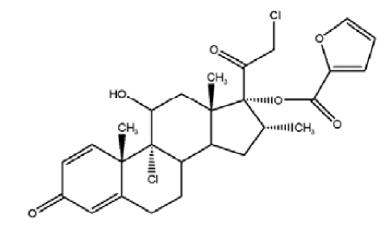 DRUG LABEL: MOMETASONE FUROATE
NDC: 60429-664 | Form: SPRAY, METERED
Manufacturer: Golden State Medical Supply, Inc.
Category: prescription | Type: HUMAN PRESCRIPTION DRUG LABEL
Date: 20250710

ACTIVE INGREDIENTS: MOMETASONE 50 ug/1 1
INACTIVE INGREDIENTS: GLYCERIN; MICROCRYSTALLINE CELLULOSE; CARBOXYMETHYLCELLULOSE SODIUM, UNSPECIFIED; SODIUM CITRATE, UNSPECIFIED FORM; CITRIC ACID MONOHYDRATE; BENZALKONIUM CHLORIDE; POLYSORBATE 80; WATER

HIGHLIGHTS OF PRESCRIBING INFORMATION

MOMETASONE FUROATE NASAL SPRAY. These highlights do not include all the information needed to use MOMETASONE FUROATE NASAL SPRAY safely and effectively. See full prescribing information for MOMETASONE FUROATE NASAL SPRAY.
MOMETASONE FUROATE Nasal Spray
Initial U.S. Approval: 1997

1 INDICATIONS AND USAGE

Mometasone furoate nasal spray is a corticosteroid indicated for:

- Prophylaxis of Nasal Symptoms of Seasonal Allergic Rhinitis in adult and pediatric patients 12 years of age and older (1.1)
- Treatment of Chronic Rhinosinusitis with Nasal Polyps in adult patients 18 years of age and older (1.2)

2 DOSAGE AND ADMINISTRATION

For Nasal Use Only

- Prophylaxis of Seasonal Allergic Rhinitis in Adult and Pediatric Patients 12 Years of Age and Older: 2 sprays in each nostril once daily (2.2)
- Treatment of Chronic Rhinosinusitis with Nasal Polyps in Adults (18 yrs. and older): 2 sprays in each nostril twice daily. 2 sprays in each nostril once daily may also be effective in some patients (2.3)

3 DOSAGE FORMS AND STRENGTHS

Nasal Spray: 50 mcg of mometasone furoate in each spray (3)

4 CONTRAINDICATIONS

Patients with known hypersensitivity to mometasone furoate or any of the ingredients of mometasone furoate nasal spray. (4)

5 WARNINGS AND PRECAUTIONS

- Epistaxis, nasal ulceration, Candida albicansinfection, nasal septal perforation, impaired wound healing. Monitor patients periodically for signs of adverse effects on the nasal mucosa. Avoid use in patients with recent nasal ulcers, nasal surgery, or nasal trauma. (5.1)
- Glaucoma and cataracts. Consider referral to an ophthalmologist in patients who develop ocular symptoms or use mometasone furoate nasal spray long term. (5.2)
- Potential worsening of existing tuberculosis; fungal, bacterial, viral, or parasitic infections; or ocular herpes simplex. More serious or even fatal course of chickenpox or measles in susceptible patients. Use caution in patients with the above because of the potential for worsening of these infections. (5.4)
- Hypercorticism and adrenal suppression with higher than recommended dosages or at the regular dosage in susceptible individuals. If such changes occur, discontinue mometasone furoate nasal spray slowly. (5.5)
- Potential reduction in growth velocity in children. Monitor growth routinely in pediatric patients receiving mometasone furoate nasal spray. (5.6, 8.4)

6 ADVERSE REACTIONS

The most common adverse reactions (incidence ≥5%) included headache, viral infection, pharyngitis, epistaxis and cough. (6)

To report SUSPECTED ADVERSE REACTIONS, contact Apotex Corp. at 1-800-706-5575or FDA at 1-800-FDA-1088 or www.fda.gov/medwatch.

FULL PRESCRIBING INFORMATION

1 INDICATIONS AND USAGE

1.1 Prophylaxis of Seasonal Allergic Rhinitis

Mometasone furoate nasal spray is indicated for the prophylaxis of the nasal symptoms of seasonal allergic rhinitis in adult and pediatric patients 12 years and older.

1.2 Treatment of Chronic Rhinosinusitis with Nasal Polyps

Mometasone furoate nasal spray is indicated for the treatment of chronic rhinosinusitis with nasal polyps in adult patients 18 years of age and older.

2 DOSAGE AND ADMINISTRATION

2.1 Preparation and Administration

Administer mometasone furoate nasal spray by the nasal route only.

Initial Priming

Prior to initial use of mometasone furoate nasal spray, the pump must be primed by actuating ten times or until a fine spray appears. The pump may be stored unused for up to 1 week without repriming.

Repriming (as needed)

If unused for more than 1 week, reprime by actuating two times, or until a fine spray appears.

2.2 Recommended Dosage for Prophylaxis of Seasonal Allergic Rhinitis

The recommended dosage for prophylaxis treatment of nasal symptoms of seasonal allergic rhinitis in adult and pediatric patients 12 years and older is mometasone furoate nasal spray 2 sprays (2 sprays deliver a total of 100 mcg of mometasone furoate) in each nostril once daily (total daily dose of 200 mcg).

In patients with a known seasonal allergen that precipitates nasal symptoms of seasonal allergic rhinitis, prophylaxis with 2 sprays (2 sprays deliver a total of 100 mcg of mometasone furoate) in each nostril once daily (total daily dose of 200 mcg) is recommended 2 to 4 weeks prior to the anticipated start of the pollen season.

2.3 Recommended Dosage for Treatment of Chronic Rhinosinusitis with Nasal Polyps

The recommended dosage for the treatment of chronic rhinosinusitis with nasal polyps in adults 18 years and older is mometasone furoate nasal spray 2 sprays (2 sprays deliver a total of 100 mcg of mometasone furoate) in each nostril twice daily (total daily dose of 400 mcg). A dose of 2 sprays (2 sprays deliver a total of 100 mcg of mometasone furoate) in each nostril once daily (total daily dose of 200 mcg) is also effective in some patients.

3 DOSAGE FORMS AND STRENGTHS

Nasal spray: 50 mcg of mometasone furoate in each spray.

4 CONTRAINDICATIONS

Mometasone furoate nasal spray is contraindicated in patients with known hypersensitivity to mometasone furoate or any of its ingredients [see Warnings and Precautions (5.3), Description (11)].

5 WARNINGS AND PRECAUTIONS

5.1 Local Nasal Adverse Reactions

Epistaxis

Epistaxis was observed more frequently in patients with allergic rhinitis and patients with chronic rhinosinusitis with nasal polyps who received mometasone furoate nasal spray than those who received placebo [see Adverse Reactions (6.1)].

CandidaInfection

Localized infections of the nose and pharynx with Candida albicans has occurred from nasal administration of mometasone furoate. When such an infection develops, use of mometasone furoate nasal spray should be discontinued and appropriate local or systemic therapy instituted, if needed.

Nasal Septum Perforation

Instances of nasal septum perforation occurred in patients following the nasal application of corticosteroids, including mometasone furoate nasal spray. As with any long-term topical treatment of the nasal cavity, patients using mometasone furoate nasal spray over several months or longer should be examined periodically for possible changes in the nasal mucosa.

Impaired Wound Healing

Because of the inhibitory effect of corticosteroids on wound healing, patients who have experienced recent nasal septum ulcers, nasal surgery, or nasal trauma should not use a nasal corticosteroid until healing has occurred.

5.2 Glaucoma and Cataracts

Glaucoma and cataracts may be reported with systemic and topical (including nasal, inhaled and ophthalmic) corticosteroid use. Consider referral to an ophthalmologist in patients who develop ocular symptoms or use mometasone furoate nasal spray long term [see Adverse Reactions (6)].

5.3 Hypersensitivity Reactions

Hypersensitivity reactions including instances of wheezing may occur after the nasal administration of mometasone furoate monohydrate. Discontinue mometasone furoate nasal spray if such reactions occur [ see Contraindications (4)] .

5.4 Immunosuppression and Risk of Infections

Persons who are on drugs which suppress the immune system are more susceptible to infections than healthy individuals. Chickenpox and measles, for example, can have a more serious or even fatal course in nonimmune children or adults on corticosteroids. In such children or adults who have not had these diseases, particular care should be taken to avoid exposure. How the dose, route, and duration of corticosteroid administration affect the risk of developing a disseminated infection is not known. The contribution of the underlying disease and/or prior corticosteroid treatment to the risk is also not known. If exposed to chickenpox, prophylaxis with varicella zoster immune globulin (VZIG) may be indicated. If exposed to measles, prophylaxis with pooled intramuscular immunoglobulin (IG) may be indicated. (See the respective Prescribing Information for VZIG and IG.) If chickenpox develops, treatment with antiviral agents may be considered.

Corticosteroids should be used with caution, if at all, in patients with active or quiescent tuberculous infection of the respiratory tract, or in untreated fungal, bacterial, systemic viral infections, or ocular herpes simplex because of the potential for worsening of these infections.

5.5 Hypercorticism and Adrenal Suppression

Hypercorticism and adrenal suppression may occur when nasal corticosteroids, including mometasone furoate nasal spray, are used at higher-than-recommended dosages [see Dosage and Administration (2)] or in patients at risk for such effects. If such changes occur, the dosage of mometasone furoate nasal spray should be discontinued slowly, consistent with accepted procedures for discontinuing oral corticosteroid therapy.

5.6 Effect on Growth

Corticosteroids, including mometasone furoate nasal spray may cause a reduction in growth velocity when administered to pediatric patients. Routinely, monitor the growth of pediatric patients receiving mometasone furoate nasal spray. To minimize the systemic effects of nasal corticosteroids, including mometasone furoate nasal spray, titrate each patient’s dose to the lowest dosage that effectively controls his/her symptoms [see Use in Specific Populations (8.4)].

6 ADVERSE REACTIONS

The following clinically significant adverse reactions are described elsewhere in labeling:

- Epistaxis, Ulcerations, Candida albicans Infection, Impaired Wound Healing [see Warnings and Precautions (5.1)]
- Glaucoma and Cataracts [see Warnings and Precautions (5.2)]
- Immunosuppression and Risk of Infections [see Warnings and Precautions (5.4)]
- Hypercorticism and Adrenal Suppression, including Growth Reduction [see Warnings and Precautions (5.5, 5.6), Use in Specific Populations (8.4)]

6.1 Clinical Trials Experience

Because clinical trials are conducted under widely varying conditions, adverse reaction rates observed in the clinical trials of a drug cannot be directly compared to rates in the clinical trials of another drug and may not reflect the rates observed in practice.

Allergic Rhinitis

Adults and pediatric patients 12 years of age and older

In controlled U.S. and international clinical studies, a total of 3,210 adult and pediatric patients 12 years and older with allergic rhinitis received treatment with mometasone furoate nasal spray at doses of 50 to 800 mcg/day. The majority of patients (n=2,103) were treated with 200 mcg/day. A total of 350 adult and pediatric patients 12 years and older have been treated for one year or longer. Adverse reactions did not differ significantly based on age, sex, or race. Four percent or less of patients in clinical trials discontinued treatment because of adverse events and the discontinuation rate was similar for the vehicle and active comparators.

All adverse reactions (regardless of relationship to treatment) reported by 5% or more of adult and pediatric patients ages 12 years and older who received mometasone furoate nasal spray, 200 mcg/day vs. placebo and that were more common with mometasone furoate nasal spray than placebo, are displayed in Table 1 below.

Table 1: Adult and Pediatric Patients 12 Years and Older – Adverse Reactions from Controlled Clinical Trials in Seasonal Allergic and Perennial Allergic Rhinitis (Percent of Patients Reporting)

 | Mometasone Furoate Nasal Spray 200 mcg (n = 2,103) % | Vehicle Placebo (n = 1,671) %
Headache | 26 | 22
Viral Infection | 14 | 11
Pharyngitis | 12 | 10
Epistaxis/Blood-Tinged Mucus | 11 | 6
Coughing | 7 | 6
Upper Respiratory Tract Infection | 6 | 2
Dysmenorrhea | 5 | 3
Musculoskeletal Pain | 5 | 3
Sinusitis | 5 | 3

Other adverse reactions which occurred in less than 5% but greater than or equal to 2% of adult and pediatric patients (ages 12 years and older) treated with mometasone furoate nasal spray 200-mcg/day (regardless of relationship to treatment), and more frequently than in the placebo group included: arthralgia, asthma, bronchitis, chest pain, conjunctivitis, diarrhea, dyspepsia, earache, flu-like symptoms, myalgia, nausea, and rhinitis.

Chronic Rhinosinusitis with Nasal Polyps

Adults 18 years of age and older

In controlled clinical studies, the types of adverse reactions observed in patients with chronic rhinosinusitis with nasal polyps were similar to those observed in patients with allergic rhinitis. A total of 594 adult patients (ages 18 to 86 years) received mometasone furoate nasal spray at doses of 200 mcg once or twice daily for up to 4 months for treatment of chronic rhinosinusitis with nasal polyps. The overall incidence of adverse reactions for patients treated with mometasone furoate nasal spray was comparable to patients with the placebo except for epistaxis, which was 9% for 200 mcg once daily, 13% for 200 mcg twice daily, and 5% for the placebo.

Nasal ulcers and nasal and oral candidiasis were also reported in patients treated with mometasone furoate nasal spray primarily in patients treated for longer than 4 weeks.

6.2 Post-Marketing Experience

The following adverse reactions have been identified during the post-marketing period for mometasone furoate nasal spray: nasal burning and irritation, anaphylaxis and angioedema, disturbances in taste and smell, nasal septal perforation, and vision blurred. Because these reactions are reported voluntarily from a population of uncertain size, it is not always possible to reliably estimate their frequency or establish a causal relationship to drug exposure.

7 DRUG INTERACTIONS

No formal drug-drug interaction studies have been conducted with mometasone furoate nasal spray.

Inhibitors of Cytochrome P450 3A4: Studies have shown that mometasone furoate is primarily and extensively metabolized in the liver of all species investigated and undergoes extensive metabolism to multiple metabolites. In vitro studies have confirmed the primary role of cytochrome CYP3A4 in the metabolism of this compound.

Concomitant administration of CYP3A4 inhibitors may inhibit the metabolism of, and increase the systemic exposure to, mometasone furoate and potentially increase the risk for systemic corticosteroid side effects. Caution should be exercised when considering the coadministration of mometasone furoate nasal spray with long-term ketoconazole and other known strong CYP3A4 inhibitors (e.g., ritonavir, cobicistat-containing products, atazanavir, clarithromycin, indinavir, itraconazole, nefazodone, nelfinavir, saquinavir, telithromycin) [see Clinical Pharmacology (12.3)]. Consider the benefit of coadministration versus the potential risk of systemic corticosteroid effects, in which case patients should be monitored for systemic corticosteroid side effects.

8 USE IN SPECIFIC POPULATIONS

8.1 Pregnancy

TERATOGENIC EFFECTS

Risk Summary

Mometasone is minimally absorbed systemically following nasal use, and maternal use is not expected to result in fetal exposure to the drug. Available data from observational studies of mometasone use in pregnant women are insufficient to evaluate for a drug-associated risk of major birth defects, miscarriage or other adverse maternal or fetal outcomes. In animal reproduction studies with pregnant mice, rats, or rabbits (subcutaneous, subcutaneous/topical dermal/oral, and topical dermal/oral, respectively), mometasone furoate caused increased fetal malformations and decreased fetal survival and growth following administration of doses that produced exposures approximately 1/3 to 8 times the maximum recommended human dose (MRHD) on a mcg/m^2or AUC basis [see Data]. However, experience with oral corticosteroids suggests that rodents are more prone to teratogenic effects from corticosteroid exposure than humans.

The estimated background risk of major birth defects and miscarriage for the indicated population is unknown. All pregnancies have a background risk of birth defect, loss, or other adverse outcomes. In the U.S. general population, the estimated risk of major birth defects and miscarriage in clinically recognized pregnancies is 2% to 4% and 15% to 20%, respectively.

Data

Animal Data

In an embryofetal development study with pregnant mice dosed throughout the period of organogenesis, mometasone furoate produced cleft palate at a dose less than the maximum recommended daily intranasal dose (MRDID) (on a mcg/m^2basis with maternal subcutaneous doses of 60 mcg/kg and above) and decreased fetal survival at approximately 2 times the MRDID (on a mcg/m^2basis with a maternal subcutaneous dose of 180 mcg/kg). No toxicity was observed with a dose that produced an exposure less than the MRDID (on a mcg/m^2basis with maternal topical dermal doses of 20 mcg/kg and above).

In an embryofetal development study with pregnant rats dosed throughout the period of organogenesis, mometasone furoate produced fetal umbilical hernia at exposures approximately 10 times the MRDID (on a mcg/m^2basis with maternal topical dermal doses of 600 mcg/kg and above) and delays in fetal ossification at a dose approximately 6 times the MRDID (on a mcg/m^2basis with maternal topical dermal doses of 300 mcg/kg and above).

In another reproductive toxicity study, pregnant rats were dosed with mometasone furoate throughout pregnancy or late in gestation. Treated animals had prolonged and difficult labor, fewer live births, lower birth weight, and reduced early pup survival at a dose less than the MRDID (on a mcg/m^2basis with a maternal subcutaneous dose of 15 mcg/kg). There were no findings at a dose less than the MRDID (on a mcg/m^2basis with a maternal subcutaneous dose of 7.5 mcg/kg).

Embryofetal development studies were conducted with pregnant rabbits dosed with mometasone furoate by either the topical dermal route or oral route throughout the period of organogenesis. In the study using the topical dermal route, mometasone furoate caused multiple malformations in fetuses (e.g., flexed front paws, gallbladder agenesis, umbilical hernia, hydrocephaly) at doses approximately 6 times the MRDID (on mcg/m^2basis with maternal topical dermal doses of 150 mcg/kg and above). In the study using the oral route, mometasone furoate caused increased fetal resorptions and cleft palate and/or head malformations (hydrocephaly and domed head) at a dose approximately 30 times of the MRDID (on a mcg/m^2basis with a maternal oral dose of 700 mcg/kg). At approximately 110 times the MRDID (on a mcg/m^2basis with a maternal oral dose of 2,800 mcg/kg), most litters were aborted or resorbed. No effects were observed at a dose approximately 6 times the MRDID (on a mcg/m^2basis with a maternal oral dose of 140 mcg/kg).

8.2 Lactation

Risk Summary

There are no available data on the presence of mometasone furoate nasal spray in human milk, the effects on the breastfed child, or the effects on milk production. However, mometasone is minimally absorbed systemically by the mother following nasal use, and breastfeeding is not expected to result in exposure of the infant to mometasone. The developmental and health benefits of breastfeeding should be considered along with the mother’s clinical need for mometasone furoate nasal spray and any potential adverse effects on the breastfed infant from mometasone furoate nasal spray or from the underlying maternal condition.

8.4 Pediatric Use

The safety and effectiveness of mometasone furoate nasal spray for prophylaxis of the nasal symptoms of seasonal allergic rhinitis in pediatric patients 12 years of age and older have been established [see Adverse Reactions (6.1) and Clinical Studies (14.1)]. Use of mometasone furoate nasal spray forthis indication is supported by evidence from controlled trials in adult and pediatric patients 12 years of age and older [see Clinical Studies (14.1)].

The safety and effectiveness of mometasone furoate nasal spray for the treatment of chronic rhinosinusitis with nasal polyps in pediatric patients less than 18 years of age have not been established. Effectiveness was not demonstrated in one 4-month trial conducted to evaluate the safety and efficacy of mometasone furoate nasal spray in the treatment of chronic rhinosinusitis with nasal polyps in pediatric patients 6 to 17 years of age. The primary objective of the study was to evaluate safety; efficacy parameters were collected as secondary endpoints. A total of 127 patients with chronic rhinosinusitis with nasal polyps were randomized to placebo or mometasone furoate nasal spray 100 mcg once or twice daily (patients 6 to 11 years of age) or 200 mcg once or twice daily (patients 12 to 17 years of age). The results of this trial did not support the efficacy of mometasone furoate nasal spray in the treatment of chronic rhinosinusitis with nasal polyps in pediatric patients. The adverse reactions reported in this trial were similar to the adverse reactions reported in patients 18 years of age and older with chronic rhinosinusitis with nasal polyps.

Effect on Growth

Controlled clinical studies have shown nasal corticosteroids may cause a reduction in growth velocity in pediatric patients. This effect has been observed in the absence of laboratory evidence of hypothalamic-pituitary-adrenal (HPA) axis suppression, suggesting that growth velocity is a more sensitive indicator of systemic corticosteroid exposure in pediatric patients than some commonly used tests of HPA axis function. The long-term effects of this reduction in growth velocity associated with nasal corticosteroids, including the impact on final adult height, are unknown. The potential for "catch up" growth following discontinuation of treatment with nasal corticosteroids has not been adequately studied. The growth of pediatric patients receiving nasal corticosteroids, including mometasone furoate nasal spray, should be monitored routinely (e.g., via stadiometry). The potential growth effects of prolonged treatment should be weighed against clinical benefits obtained and the availability of safe and effective noncorticosteroid treatment alternatives. To minimize the systemic effects of nasal corticosteroids, including mometasone furoate nasal spray, each patient should be titrated to his/her lowest effective dose.

A clinical study to assess the effect of mometasone furoate nasal spray (100 mcg total daily dose) on growth velocity has been conducted in pediatric patients 3 to 9 years of age with allergic rhinitis. No statistically significant effect on growth velocity was observed for mometasone furoate nasal spray compared to placebo following one year of treatment. No evidence of clinically relevant HPA axis suppression was observed following a 30-minute cosyntropin infusion.

The potential of mometasone furoate nasal spray to cause growth suppression in susceptible patients or when given at higher doses cannot be ruled out.

8.5 Geriatric Use

A total of 280 patients above 64 years of age with allergic rhinitis or chronic rhinosinusitis with nasal polyps (age range 64 to 86 years) have been treated with mometasone furoate nasal spray for up to 3 or 4 months, respectively. No observed differences in safety and/or effectiveness in geriatric patients compared to younger adult patients.

8.6 Hepatic Impairment

Concentrations of mometasone furoate appear to increase with severity of hepatic impairment [see Clinical Pharmacology (12.3)] .

10 OVERDOSAGE

There are no data available on the effects of acute or chronic overdosage with mometasone furoate nasal spray. Because of low systemic bioavailability, and an absence of acute drug-related systemic findings in clinical studies, overdose is unlikely to require any therapy other than observation. Chronic overdosage with any corticosteroid may result in signs or symptoms of hypercorticism. [ see Warnings and Precautions (5.5) ].

11 DESCRIPTION

Mometasone furoate, the active component of mometasone furoate nasal spray, 50 mcg, is an anti-inflammatory corticosteroid having the chemical name, 9,21-Dichloro-11ß,17-dihydroxy-16α-methylpregna-1,4-diene-3,20-dione17-(2 furoate), and the following chemical structure:

Mometasone furoate is a white to off-white powder, with an molecular formula of C27H30Cl2O6, and a molecular weight of 521.43. It is practically insoluble in water, slightly soluble in methanol, ethanol, and isopropanol; soluble in acetone, chloroform, and methylene chloride; and freely soluble in tetrahydrofuran, acetone and dichloromethane. Its partition coefficient between octanol and water is greater than 5,000.

Mometasone furoate nasal spray 50 mcg is a metered-dose, manual pump spray unit containing an aqueous suspension of 0.05% w/w mometasone furoate in an aqueous medium containing benzalkonium chloride, citric acid, glycerin, microcrystalline cellulose and carboxymethylcellulose sodium, polysorbate 80, purified water, and sodium citrate. The pH is between 4.3 and 4.9.

12 CLINICAL PHARMACOLOGY

12.1 Mechanism of Action

Mometasone furoate nasal spray is a corticosteroid demonstrating potent anti-inflammatory properties. The precise mechanism of corticosteroid action on allergic rhinitis is not known. Corticosteroids have been shown to have a wide range of effects on multiple cell types (e.g., mast cells, eosinophils, neutrophils, macrophages, and lymphocytes) and mediators (e.g., histamine, eicosanoids, leukotrienes, and cytokines) involved in inflammation.

In two clinical studies utilizing nasal antigen challenge, mometasone furoate nasal spray decreased some markers of the early- and late-phase allergic response. These observations included decreases (vs. placebo) in histamine and eosinophil cationic protein levels, and reductions (vs. baseline) in eosinophils, neutrophils, and epithelial cell adhesion proteins. The clinical significance of these findings is not known.

The effect of mometasone furoate nasal spray on nasal mucosa following 12 months of treatment was examined in 46 patients with allergic rhinitis. There was no evidence of atrophy and there was a marked reduction in intraepithelial eosinophilia and inflammatory cell infiltration (e.g., eosinophils, lymphocytes, monocytes, neutrophils, and plasma cells).

12.2 Pharmacodynamics

Adrenal Function in Adults: Four clinical pharmacology studies have been conducted in humans to assess the effect of mometasone furoate nasal spray at various doses on adrenal function. In one study, daily doses of 200 and 400 mcg of mometasone furoate nasal spray and 10 mg of prednisone were compared to placebo in 64 patients (22 to 44 years of age) with allergic rhinitis. Adrenal function before and after 36 consecutive days of treatment was assessed by measuring plasma cortisol levels following a 6-hour Cortrosyn (ACTH) infusion and by measuring 24-hour urinary free cortisol levels. Mometasone furoate nasal spray at both the 200- and 400-mcg dose, was not associated with a statistically significant decrease in mean plasma cortisol levels post-Cortrosyn infusion or a statistically significant decrease in the 24-hour urinary free cortisol levels compared to placebo. A statistically significant decrease in the mean plasma cortisol levels post-Cortrosyn infusion and 24-hour urinary free cortisol levels was detected in the prednisone treatment group compared to placebo.

A second study assessed adrenal response to mometasone furoate nasal spray (400 and 1,600 mcg/day), prednisone (10 mg/day), and placebo, administered for 29 days in 48 male volunteers (21 to 40 years of age). The 24-hour plasma cortisol area under the curve (AUC0–24), during and after an 8-hour Cortrosyn infusion and 24-hour urinary free cortisol levels were determined at baseline and after 29 days of treatment. No statistically significant differences in adrenal function were observed with mometasone furoate nasal spray compared to placebo.

A third study evaluated single, rising doses of mometasone furoate nasal spray (1,000, 2,000, and 4,000 mcg/day), orally administered mometasone furoate (2,000, 4,000, and 8,000 mcg/day), orally administered dexamethasone (200, 400, and 800 mcg/day), and placebo (administered at the end of each series of doses) in 24 male volunteers (22 to 39 years of age). Dose administrations were separated by at least 72 hours. Determination of serial plasma cortisol levels at 8 AM and for the 24-hour period following each treatment were used to calculate the plasma cortisol area under the curve (AUC0–24). In addition, 24-hour urinary free cortisol levels were collected prior to initial treatment administration and during the period immediately following each dose. No statistically significant decreases in the plasma cortisol AUC, 8 AM cortisol levels, or 24-hour urinary free cortisol levels were observed in volunteers treated with either mometasone furoate nasal spray or oral mometasone, as compared with placebo treatment. Conversely, nearly all volunteers treated with the three doses of dexamethasone demonstrated abnormal 8 AM cortisol levels (defined as a cortisol level <10 mcg/dL), reduced 24-hour plasma AUC values, and decreased 24-hour urinary free cortisol levels, as compared to placebo treatment.

In a fourth study, adrenal function was assessed in 213 patients (18 to 81 years of age) with chronic rhinosinusitis with nasal polyps before and after 4 months of treatment with either mometasone furoate nasal spray (200 mcg once or twice daily) or placebo by measuring 24-hour urinary free cortisol levels. Mometasone furoate nasal spray at both doses (200 and 400 mcg/day), was not associated with statistically significant decreases in the 24-hour urinary free cortisol levels compared to placebo.

Three clinical pharmacology studies have been conducted in pediatric patients to assess the effect of mometasone furoate nasal spray on the adrenal function at daily doses of 50, 100, and 200 mcg vs. placebo. In one study, adrenal function before and after 7 consecutive days of treatment was assessed in 48 pediatric patients with allergic rhinitis (ages 6 to 11 years) by measuring morning plasma cortisol and 24-hour urinary free cortisol levels. Mometasone furoate nasal spray, at all three doses, was not associated with a statistically significant decrease in mean plasma cortisol levels or a statistically significant decrease in the 24-hour urinary free cortisol levels compared to placebo. In the second study, adrenal function before and after 14 consecutive days of treatment was assessed in 48 pediatric patients (ages 3 to 5 years) with allergic rhinitis by measuring plasma cortisol levels following a 30-minute Cortrosyn infusion. Mometasone furoate nasal spray, 50 mcg, at all three doses (50, 100, and 200 mcg/day), was not associated with a statistically significant decrease in mean plasma cortisol levels post-Cortrosyn infusion compared to placebo. All patients had a normal response to Cortrosyn. In the third study, adrenal function before and after up to 42 consecutive days of once-daily treatment was assessed in 52 patients with allergic rhinitis (ages 2 to 5 years), 28 of whom received mometasone furoate nasal spray, 50 mcg per nostril (total daily dose 100 mcg), by measuring morning plasma cortisol and 24-hour urinary free cortisol levels. Mometasone furoate nasal spray was not associated with a statistically significant decrease in mean plasma cortisol levels or a statistically significant decrease in the 24-hour urinary free cortisol levels compared to placebo.

12.3 Pharmacokinetics

Absorption:

Mometasone furoate monohydrate administered as a nasal spray suspension has very low bioavailability (<1%) in plasma using a sensitive assay with a lower quantitation limit (LOQ) of 0.25 pcg/mL.

Distribution:

The in vitroprotein binding for mometasone furoate was reported to be 98% to 99% in concentration range of 5 to 500 ng/mL.

Elimination:

Following intravenous administration, the effective plasma elimination half-life of mometasone furoate is 5.8 hours. Any absorbed drug is excreted as metabolites mostly via the bile, and to a limited extent, into the urine.

Metabolism:

Studies have shown that any portion of a mometasone furoate dose which is swallowed and absorbed undergoes extensive metabolism to multiple metabolites. There are no major metabolites detectable in plasma. Upon in vitro incubation, one of the minor metabolites formed is 6ß-hydroxymometasone furoate. In human liver microsomes, the formation of the metabolite is regulated by cytochrome P-450 3A4 (CYP3A4).

Specific Populations:

Patients with Hepatic Impairment:

Administration of a single inhaled dose of 400 mcg mometasone furoate to subjects with mild (n=4), moderate (n=4), and severe (n=4) hepatic impairment resulted in only 1 or 2 subjects in each group having detectable peak plasma concentrations of mometasone furoate (ranging from 50 to 105 pcg/mL). The observed peak plasma concentrations appear to increase with severity of hepatic impairment, however, the numbers of detectable levels were few.

Patients with Renal Impairment:

The effects of renal impairment on mometasone furoate pharmacokinetics have not been adequately investigated.

Pediatric Patients:

Mometasone furoate pharmacokinetics have not been investigated in the pediatric population [ see Use in Specific Populations (8.4)].

Male and Female Patients:

The effects of gender on mometasone furoate pharmacokinetics have not been adequately investigated.

Racial or Ethnic Groups:

The effects of race on mometasone furoate pharmacokinetics have not been adequately investigated.

Drug Interaction Studies:

Inhibitors of Cytochrome P450 3A4: In a drug interaction study, an inhaled dose of mometasone furoate 400 mcg was given to 24 healthy subjects twice daily for 9 days and ketoconazole 200 mg (as well as placebo) were given twice daily concomitantly on Days 4 to 9. Mometasone furoate plasma concentrations were <150 pcg/mL on Day 3 prior to coadministration of ketoconazole or placebo. Following concomitant administration of ketoconazole, 4 out of 12 subjects in the ketoconazole treatment group (n=12) had peak plasma concentrations of mometasone furoate >200 pcg/mL on Day 9 (211 to 324 pcg/mL).

13 NONCLINICAL TOXICOLOGY

13.1 Carcinogenesis, Mutagenesis, Impairment of Fertility

In a 2-year carcinogenicity study in Sprague Dawley rats, mometasone furoate demonstrated no statistically significant increase in the incidence of tumors at inhalation doses up to 67 mcg/kg (approximately 1 and 2 times the maximum recommended daily nasal dose [MRDID] in adults [400 mcg] and children [100 mcg], respectively, on a mcg/m^2basis). In a 19-month carcinogenicity study in Swiss CD-1 mice, mometasone furoate demonstrated no statistically significant increase in the incidence of tumors at inhalation doses up to 160 mcg/kg (approximately 2 times the MRDID in adults and children, respectively, on a mcg/m^2basis).

Mometasone furoate increased chromosomal aberrations in an in vitroChinese hamster ovary-cell assay, but did not increase chromosomal aberrations in an in vitroChinese hamster lung cell assay. Mometasone furoate was not mutagenic in the Ames test or mouse-lymphoma assay, and was not clastogenic in an in vivomouse micronucleus assay and a rat bone marrow chromosomal aberration assay or a mouse male germ-cell chromosomal aberration assay. Mometasone furoate also did not induce unscheduled DNA synthesis in vivoin rat hepatocytes.

In reproductive studies in rats, impairment of fertility was not produced by subcutaneous doses up to 15 mcg/kg (less than the MRDID in adults on a mcg/m^2basis).

13.2 Animal Toxicology and/or Pharmacology

Reproduction Toxicology Studies

In mice, mometasone furoate caused cleft palate at subcutaneous doses of 60 mcg/kg and above (less than the MRDID in adults on a mcg/m^2basis). Fetal survival was reduced at 180 mcg/kg (approximately 2 times the MRDID in adults on a mcg/m^2basis). No toxicity was observed at 20 mcg/kg (less than the MRDID in adults on a mcg/m^2basis).

In rats, mometasone furoate produced umbilical hernia at topical dermal doses of 600 mcg/kg and above (approximately 10 times the MRDID in adults on a mcg/m^2basis). A dose of 300 mcg/kg (approximately 6 times the MRDID in adults on a mcg/m^2basis) produced delays in ossification, but no malformations. In rabbits, mometasone furoate caused multiple malformations (e.g., flexed front paws, gallbladder agenesis, umbilical hernia, hydrocephaly) at topical dermal doses of 150 mcg/kg and above (approximately 6 times the MRDID in adults on a mcg/m^2basis). In an oral study, mometasone furoate increased resorptions and caused cleft palate and/or head malformations (hydrocephaly or domed head) at 700 mcg/kg (approximately 30 times the MRDID in adults on a mcg/m^2basis). At 2,800 mcg/kg (approximately 110 times the MRDID in adults on a mcg/m^2basis), most litters were aborted or resorbed. No toxicity was observed at 140 mcg/kg (approximately 6 times the MRDID in adults on a mcg/m^2basis).

When rats received subcutaneous doses of mometasone furoate throughout pregnancy or during the later stages of pregnancy, 15 mcg/kg (less than the MRDID in adults on a mcg/m^2basis) caused prolonged and difficult labor and reduced the number of live births, birth weight, and early pup survival. Similar effects were not observed at 7.5 mcg/kg (less than the MRDID in adults on a mcg/m^2basis).

14 CLINICAL STUDIES

14.1 Prophylaxis of Seasonal Allergic Rhinitis in Adult and Pediatric Patients 12 Years of Age and Older

The efficacy and safety of mometasone furoate nasal spray in the prophylaxis and treatment of seasonal allergic rhinitis and the treatment of perennial allergic rhinitis have been evaluated in 18 controlled trials, and one uncontrolled clinical trial, in approximately 3,000 adults (ages 17 to 85 years) and pediatric patients (ages 12 to 16 years). Of the total number of patients, there were 1,757 males and 1,453 females, including a total of 283 adolescents (182 boys and 101 girls) with seasonal allergic or perennial allergic rhinitis. Patients were treated with mometasone furoate nasal spray at doses ranging from 50 to 800 mcg/day. The majority of patients were treated with 200 mcg/day. The allergic rhinitis trials evaluated the total nasal symptom scores that included stuffiness, rhinorrhea, itching, and sneezing. Patients treated with mometasone furoate nasal spray 200 mcg/day had a statistically significant decrease in total nasal symptom scores compared to placebo-treated patients. No additional benefit was observed for mometasone furoate doses greater than 200 mcg/day. A total of 350 patients have been treated with mometasone furoate nasal spray for 1 year or longer.

Prophylaxis of seasonal allergic rhinitis for patients 12 years of age and older with mometasone furoate nasal spray given at a dose of 200 mcg/day, was evaluated in two clinical studies in 284 patients. These studies were designed such that patients received 4 weeks of prophylaxis with mometasone furoate nasal spray prior to the anticipated onset of the pollen season; however, some patients received only 2 to 3 weeks of prophylaxis. Patients receiving 2 to 4 weeks of prophylaxis with mometasone furoate nasal spray demonstrated a statistically significantly smaller mean increase in total nasal symptom scores with onset of the pollen season as compared to placebo patients.

14.2 Chronic Rhinosinusitis with Nasal Polyps in Adults 18 Years of Age and Older

Two studies were performed to evaluate the efficacy and safety of mometasone furoate nasal spray in the treatment of chronic rhinosinusitis with nasal polyps. These studies involved 664 patients with chronic rhinosinusitis with nasal polyps, 441 of whom received mometasone furoate nasal spray. These studies were randomized, double-blind, placebo-controlled, parallel-group, multicenter studies in patients 18 to 86 years of age with bilateral nasal polyps. Patients were randomized to receive mometasone furoate nasal spray 200 mcg once daily, 200 mcg twice daily or placebo for a period of 4 months. The co-primary efficacy endpoints were 1) change from baseline in nasal congestion/obstruction averaged over the first month of treatment; and 2) change from baseline to last assessment in bilateral polyp grade during the entire 4 months of treatment as assessed by endoscopy. Efficacy was demonstrated in both studies at a dose of 200 mcg twice daily and in one study at a dose of 200 mcg once a day (see Table 2 below).

Table 2: Effect of Mometasone Furoate Nasal Spray in Two Randomized, Placebo-Controlled Trials in Patients with Chronic Rhinosinusitiswith Nasal Polyps

 | Mometasone Furoate Nasal Spray 200 mcg qd | Mometasone Furoate Nasal Spray 200 mcg bid | Placebo | P-value for Mometasone Furoate Nasal Spray 200 mcg qd vs. placebo | P-value for Mometasone Furoate Nasal Spray 200 mcg bid vs. placebo
Study 1 | N=115 | N=122 | N=117
Baseline bilateral polyp grade* | 4.21 | 4.27 | 4.25
Mean change from baseline in bilateral polyps grade | -1.15 | -0.96 | -0.50 | <0.001 | 0.01
Baseline nasal congestion† | 2.29 | 2.35 | 2.28
Mean change from baseline in nasal congestion | -0.47 | -0.61 | -0.24 | 0.001 | <0.001
Study 2 | N=102 | N=102 | N=106
Baseline bilateral polyp grade* | 4.00 | 4.10 | 4.17
Mean change from baseline in bilateral polyps grade | -0.78 | -0.96 | -0.62 | 0.33 | 0.04
Baseline nasal congestion† | 2.23 | 2.20 | 2.18
Mean change from baseline in nasal congestion | -0.42 | -0.66 | -0.23 | 0.01 | <0.001

* polyps in each nasal fossa were graded by the investigator based on endoscopic visualization, using a scale of 0-3 where 0=no polyps; 1=polyps in the middle meatus, not reaching below the inferior border of the middle turbinate; 2=polyps reaching below the inferior border of the middle turbinate but not the inferior border of the inferior turbinate; 3=polyps reaching to or below the border of the inferior turbinate, or polyps medial to the middle turbinate (score reflects sum of left and right nasal fossa grades).

†nasal congestion/obstruction was scored daily by the patient using a 0-3 categorical scale where 0=no symptoms, 1=mild symptoms, 2=moderate symptoms and 3=severe symptoms.

There were no clinically relevant differences in the effectiveness of mometasone furoate nasal spray in the studies evaluating treatment of chronic rhinosinusitis with nasal polyps across subgroups of patients defined by gender, age, or race.

16 HOW SUPPLIED/STORAGE AND HANDLING

STORAGE AND HANDLING

Mometasone Furoate Nasal Spray:

- 50 mcg mometasone furoate per spray
- is supplied in a white, high-density, polyethylene bottle fitted with a white metered-dose, manual spray pump, and translucent cap
- contains 17 g of product formulation (NDC 60429-664-17)
- 120 sprays, each delivering 50 mcg of mometasone furoate per actuation

Store at 20°C to 25°C (68°F to 77°F) [see USP Controlled Room Temperature]. Protect from light.

When mometasone furoate nasal spray is removed from its cardboard container, prolonged exposure of the product to direct light should be avoided. Brief exposure to light, as with normal use, is acceptable.

SHAKE WELL BEFORE EACH USE.

17 PATIENT COUNSELING INFORMATION

Advise the patient to read the FDA-approved patient labeling (Patient Information and Instructions for Use).

Local Nasal Adverse Reactions

Patients should be informed that treatment with mometasone furoate nasal spray may be associated with adverse reactions which include epistaxis (nose bleed) and nasal septum perforation. Candida infection may also occur. Because of the inhibitory effect of corticosteroids on wound healing, patients who have experienced recent nasal septum ulcers, nasal surgery, or nasal trauma should not use a nasal corticosteroid until healing has occurred [ see Warnings and Precautions (5.1)]. Patients should be cautioned not to spray mometasone furoate nasal spray directly onto the nasal septum.

Glaucoma and Cataracts

Advise patients that long-term use of nasal and inhaled corticosteroids may increase the risk of some eye problems (glaucoma or cataracts); regular eye examinations should be considered. Patients should be cautioned not to spray mometasone furoate nasal spray into the eyes [ see Warnings and Precautions (5.2) ].

Immunosuppression and Risk of Infections

Persons who are on immunosuppressant doses of corticosteroids should be warned to avoid exposure to chickenpox or measles, and patients should also be advised that if they are exposed, medical advice should be sought without delay [ see Warnings and Precautions (5.4)].

Use Regularly for Best Effect

Patients should use mometasone furoate nasal spray on a regular basis for optimal effect. Improvement in nasal symptoms of allergic rhinitis has been shown to occur within 1 to 2 days after initiation of dosing. Maximum benefit is usually achieved within 1 to 2 weeks after initiation of dosing. Patients should not increase the prescribed dosage but should contact their physician if symptoms do not improve, or if the condition worsens. Administration to young children should be aided by an adult.

If a patient missed a dose, the patient should be advised to administer the dose as soon as they remember. The patient should not use more than the recommended dose for the day.

APOTEX INC.

MOMETASONE FUROATE NASAL SPRAY

50 mcg

Marketed by:

GSMS, Inc.

Camarillo, CA 93012 USA

Manufactured by: |  |  |  |  |  |  |  |  |  |  |  |  |  |  |  |  |  |  |  |  |  |  |  |  |  |  |  |  |  |  |  |  |  |  |  |  |  |  |  |  |  |  |  |  |  |  |  |  |  |  | Manufactured for:
Apotex Inc. |  |  |  |  |  |  |  |  |  |  |  |  |  |  |  |  |  |  |  |  |  |  |  |  |  |  |  |  |  |  |  |  |  |  |  |  |  |  |  |  |  |  |  |  |  |  |  |  |  |  | Apotex Corp.
Toronto, Ontario |  |  |  |  |  |  |  |  |  |  |  |  |  |  |  |  |  |  |  |  |  |  |  |  |  |  |  |  |  |  |  |  |  |  |  |  |  |  |  |  |  |  |  |  |  |  |  |  |  |  | Weston, FL
M9L 1T9 |  |  |  |  |  |  |  |  |  |  |  |  |  |  |  |  |  |  |  |  |  |  |  |  |  |  |  |  |  |  |  |  |  |  |  |  |  |  |  |  |  |  |  |  |  |  |  |  |  |  | 33326

PATIENT INFORMATION

Mometasone Furoate(moe met' a sone fure' oh ate) Nasal Spray, 50 mcg

For Nasal Use Only

Read the Patient Information that comes with mometasone furoate nasal spray before you start using it and each time you get a refill. There may be new information. This Patient Information does not take the place of talking to your healthcare provider about your medical condition or treatment. If you have any questions about mometasone furoate nasal spray, ask your healthcare provider.

What is mometasone furoate nasal spray?

Mometasone furoate nasal spray is a man-made (synthetic) corticosteroid medicine that is used to:

- prevent nasal symptoms of seasonal allergic rhinitis in people 12 years of age and older.
- treat chronic rhinosinusitis with nasal polyps in people 18 years and older.

It is not known if mometasone furoate nasal spray is safe and effective in children under:

- 12 years of age to prevent nasal symptoms of seasonal allergic rhinitis.
- 18 years of age to treat chronic rhinosinusitis with nasal polyps.

Who should not use mometasone furoate nasal spray?

Do not usemometasone furoate nasal spray if you are allergic to mometasone furoate or any of the ingredients in mometasone furoate nasal spray. See the end of this leaflet for a complete list of ingredients in mometasone furoate nasal spray.

What should I tell my healthcare provider before and during treatment withmometasone furoate nasal spray?

Before you take mometasone furoate nasal spray, tell your healthcare provider about all of your medical conditions, including if you:

- have had recent nasal sores, nasal surgery, or nasal injury.
- have eye or vision problems, such as cataracts, glaucoma (increased pressure in your eye), and blurred vision, or other changes in your vision.
- have tuberculosis or any untreated fungal, bacterial, viral infections, or eye infections caused by herpes.
- have been near someone who has chickenpox or measles.
- are not feeling well or have any other symptoms that you do not understand.
- are pregnant or planning to become pregnant.It is not known if mometasone furoate nasal spray will harm your unborn baby. Talk to your healthcare provider if you are pregnant or plan to become pregnant.
- are breastfeeding or planning to breastfeed.It is not known whether mometasone furoate passes into your breast milk.

Tell your healthcare provider about all the medicines you takeincluding prescription and over-the-counter medicines, vitamins, and herbal supplements.

Especially tell your healthcare provider if you take:

- certain medicines for HIV (such as ritonavir, atazanavir, indinavir, nelfinavir, and saquinavir)
- cobicistat-containing products
- certain antifungals (such as ketoconazole and itraconazole)
- certain antibiotics (such as clarithromycin and telithromycin)
- certain antidepressants (such as nefazodone)
  If you take these medicines with mometasone furoate nasal spray, your healthcare provider should monitor you for side effects.
  Mometasone furoate nasal spray may affect the way other medicines work, and other medicines may affect how mometasone furoate nasal spray works.
  Know the medicines you take. Keep a list of them to show your healthcare provider and pharmacist when you get a new medicine.

How should I use mometasone furoate nasal spray?

- Use mometasone furoate nasal spray exactly as prescribed by your healthcare provider.
- This medicine is for use in the nose only.Do not spray it into your mouth or eyes.
- An adult should supervise a child using this medicine.
- For best results, you should keep using mometasone furoate nasal spray regularly each day without missing a dose. If you do miss a dose of mometasone furoate nasal spray, take it as soon as you remember. However, do not take more than the daily dose prescribed by your healthcare provider.
- Do not use mometasone furoate nasal spray more often than prescribed. Ask your healthcare provider if you have any questions.
- For detailed instructions on how to use mometasone furoate nasal spray, see the " Patient Instructions for Use" at the end of this leaflet.
- See your healthcare provider regularly to check your symptoms while taking mometasone furoate nasal spray and to check for side effects.

What should I avoid while taking mometasone furoate nasal spray?

If you are taking other corticosteroid medicines for allergy, by mouth or injection, your healthcare provider may advise you to stop taking them after you begin using mometasone furoate nasal spray.

What are the possible side effects of mometasone furoate nasal spray?

Mometasone furoate nasal spraymay cause serious side effects, including:

- thrush (candida), a fungal infection in your nose and throat.Tell your healthcare provider if you have any redness or white colored patches in your nose or throat.
- hole in the cartilage of the nose (nasal septal perforation).A whistling sound when you breathe may be a symptom of nasal septum perforation.
- slow wound healing. Do notuse mometasone furoate nasal spray until your nose has healed if you have a sore in your nose, if you have surgery on your nose, or if your nose has been injured.
- eye problems, including glaucoma, cataracts, and blurred vision.You should have regular eye exams.
- allergic reactions.Allergic reactions including wheezing may happen after usingmometasone furoate nasal spray. If wheezing happens stop using mometasone furoate nasal spray. Tell your healthcare provider or get medical help right away .
- immune system problems that may increase your risk of infections.You are more likely to get infections if you take medicines that weaken your immune system. Avoid contact with people who have contagious diseases such as chicken pox or measles while using mometasone furoate nasal spray. Symptoms of infection may include: fever, pain, aches, chills, feeling tired, nausea, and vomiting. Tell your healthcare provider about any signs of infection while you are using mometasone furoate nasal spray.
- adrenal insufficiency.Adrenal insufficiency is a condition in which the adrenal glands do not make enough steroid hormones. Symptoms of adrenal insufficiency can include: tiredness, weakness, nausea and vomiting, and low blood pressure.
- slowed growth in children. Your child’s growth should be checked regularly while using mometasone furoate nasal spray.

The most common side effects of mometasone furoate nasal spray include:

- headache
- viral infection
- sore throat
- nosebleeds
- cough

These are not all the possible side effects of mometasone furoate nasal spray. Call your healthcare provider for medical advice about side effects. You may report side effects to FDA at 1-800-FDA-1088.

How should I store mometasone furoate nasal spray?

- Store mometasone furoate nasal spray at 20°C to 25°C (68°F to 77°F) [See USP Controlled Room Temperature].
- Protect from light.
- Avoid prolonged exposure of mometasone furoate nasal spray container to direct light.
- Shake well before each use.
- Keep mometasone furoate nasal spray and all medicines out of the reach of children.

General information about the safe and effective use ofmometasone furoate nasal spray

Medicines are sometimes prescribed for conditions that are not listed in a Patient Information leaflet. Do not use mometasone furoate nasal spray for a condition for which it was not prescribed. Do not give mometasone furoate nasal spray to other people even if they have the same symptoms you have. It may harm them.

You can ask your healthcare provider or pharmacist for information about mometasone furoate nasal spray that is written for health professionals.

What are the ingredients in mometasone furoate nasal spray?

Active ingredients:mometasone furoate

Inactive ingredients:benzalkonium chloride, citric acid, glycerin, microcrystalline cellulose and carboxymethylcellulose sodium, polysorbate 80, purified water, and sodium citrate.

For more information, go to www.apotex.com/products or call 1-800-706-5575.

This Patient Information has been approved by the U.S. Food and Drug Administration

APOTEX INC.

MOMETASONE FUROATE NASAL SPRAY

50 mcg

Manufactured by: | Manufactured for:
Apotex Inc. Toronto, Ontario M9L 1T9 | Apotex Corp. Weston, FL 33326

Marketed by:

GSMS, Inc.

Camarillo, CA 93012 USA

Patient Instructions for Use

Mometasone Furoate(moe met' a sone fure' oh ate) Nasal Spray, 50 mcg

For use in your nose only.

Read the Patient Instructions for Use carefully before you start to use your mometasone furoate nasal spray. If you have any questions, ask your healthcare provider.

Shake the bottle well before each use.

- Remove the plastic cap (SeeFigure 1).

- Before you use mometasone furoate nasal spray for the first time, prime the pump by pressing downward on the shoulders of the white nasal applicator using your index finger and middle finger while holding the base of the bottle with your thumb (SeeFigure 2). Do Notpierce the nasal applicator. Press down and release the pump 10 times or until a fine spray appears. Do Notspray into eyes. The pump is now ready to use. The pump may be stored unused for up to 1 week without repriming. If unused for more than 1 week, reprime by spraying 2 times or until a fine spray appears.

- Gently blow your nose to clear the nostrils. Close 1 nostril. Tilt your head forward slightly, keep the bottle upright, carefully insert the nasal applicator into the other nostril (SeeFigure 3). Do Notspray directly onto the nasal septum (the wall between the two nostrils).

- For each spray, hold the spray bottle upright and press firmly downward 1 time on the shoulders of the white nasal applicator using your index and middle fingers while supporting the base of the bottle with your thumb. Breathe gently inward through the nostril (SeeFigure 4).
- Note: It is important to keep the Mometasone Furoate Nasal Spray unit in an upright orientation (as seen in Figure 4). Failure to do so may result in an incomplete or non-existent spray.

- Then breathe out through the mouth.

- Repeat in the other nostril.

- Wipe the nasal applicator with a clean tissue and replace the plastic cap.

Each bottle of mometasone furoate nasal spray contains enough medicine for you to spray medicine from the bottle 120 times. Do not use the bottle of mometasone furoate nasal spray after 120 sprays. Additional sprays after the 120 sprays may not contain the right amount of medicine, you should keep track of the number of sprays used from each bottle of mometasone furoate nasal spray,and throw away the bottle even if it has medicine still left in. Do not count any sprays used for priming the device.Talk with your healthcare provider before your supply runs out to see if you should get a refill of your medicine.

Pediatric Use:Administration to children should be supervised by an adult. Steps 1 through 7 from the Patient Instructions for Useshould be followed.

Cleaning: Do not try to unblock the nasal applicator with a sharp object.Please see Patient Instructions for Cleaning Applicator.

Patient Instructions for Cleaning Applicator

- To clean the nasal applicator, remove the plastic cap (SeeFigure 5).

- Pull gently upward on the white nasal applicator to remove (SeeFigure 6).

- Soak the nasal applicator in cold tap water and rinse both ends of the nasal applicator under cold tap water and dry (SeeFigure 7). Do not try to unblock the nasal applicator by inserting a pin or other sharp object as this will damage the applicator and cause you not to get the right dose of medicine.

- Rinse the plastic cap under cold water and dry (SeeFigure 8).

- Put the nasal applicator back together making sure the pump stem is reinserted into the applicator's center hole (SeeFigure 9).

- Reprime the pump by pressing downward on the shoulders of the white nasal applicator using your index and middle fingers while holding the base of the bottle with your thumb. Press down and release the pump 2 times or until a fine spray appears. Do Notspray into eyes. The pump is now ready to use. The pump may be stored unused for up to 1 week without repriming. If unused for more than 1 week, reprime by spraying 2 times or until a fine spray appears (SeeFigure 10).

- Replace the plastic cap (SeeFigure 11).

This Patient Information and Instructions for Use has been approved by the U.S. Food and Drug Administration.

APOTEX INC.

MOMETASONE FUROATE NASAL SPRAY

50 mcg

Manufactured by: |  |  |  |  |  |  |  |  |  |  |  |  |  |  |  |  |  |  |  |  |  |  |  |  |  |  |  |  |  |  |  |  |  |  |  |  |  |  |  |  |  |  |  |  |  |  |  |  |  |  | Manufactured for:
Apotex Inc. |  |  |  |  |  |  |  |  |  |  |  |  |  |  |  |  |  |  |  |  |  |  |  |  |  |  |  |  |  |  |  |  |  |  |  |  |  |  |  |  |  |  |  |  |  |  |  |  |  |  | Apotex Corp.
Toronto, Ontario |  |  |  |  |  |  |  |  |  |  |  |  |  |  |  |  |  |  |  |  |  |  |  |  |  |  |  |  |  |  |  |  |  |  |  |  |  |  |  |  |  |  |  |  |  |  |  |  |  |  | Weston, FL
M9L 1T9 |  |  |  |  |  |  |  |  |  |  |  |  |  |  |  |  |  |  |  |  |  |  |  |  |  |  |  |  |  |  |  |  |  |  |  |  |  |  |  |  |  |  |  |  |  |  |  |  |  |  | 33326

Revised: March 2025

Marketed by:

GSMS, Inc.

Camarillo, CA 93012 USA

PRINCIPAL DISPLAY PANEL - Bottle Label

NDC 60429-664-17

Net Contents: 17 g

120 Metered Sprays

For Intranasal Use Only

Rx Only

PRINCIPAL DISPLAY PANEL - Carton Label

NDC 60429-664-17

Net Contents: 17 g

120 Metered Sprays

For Intranasal Use Only

Rx Only